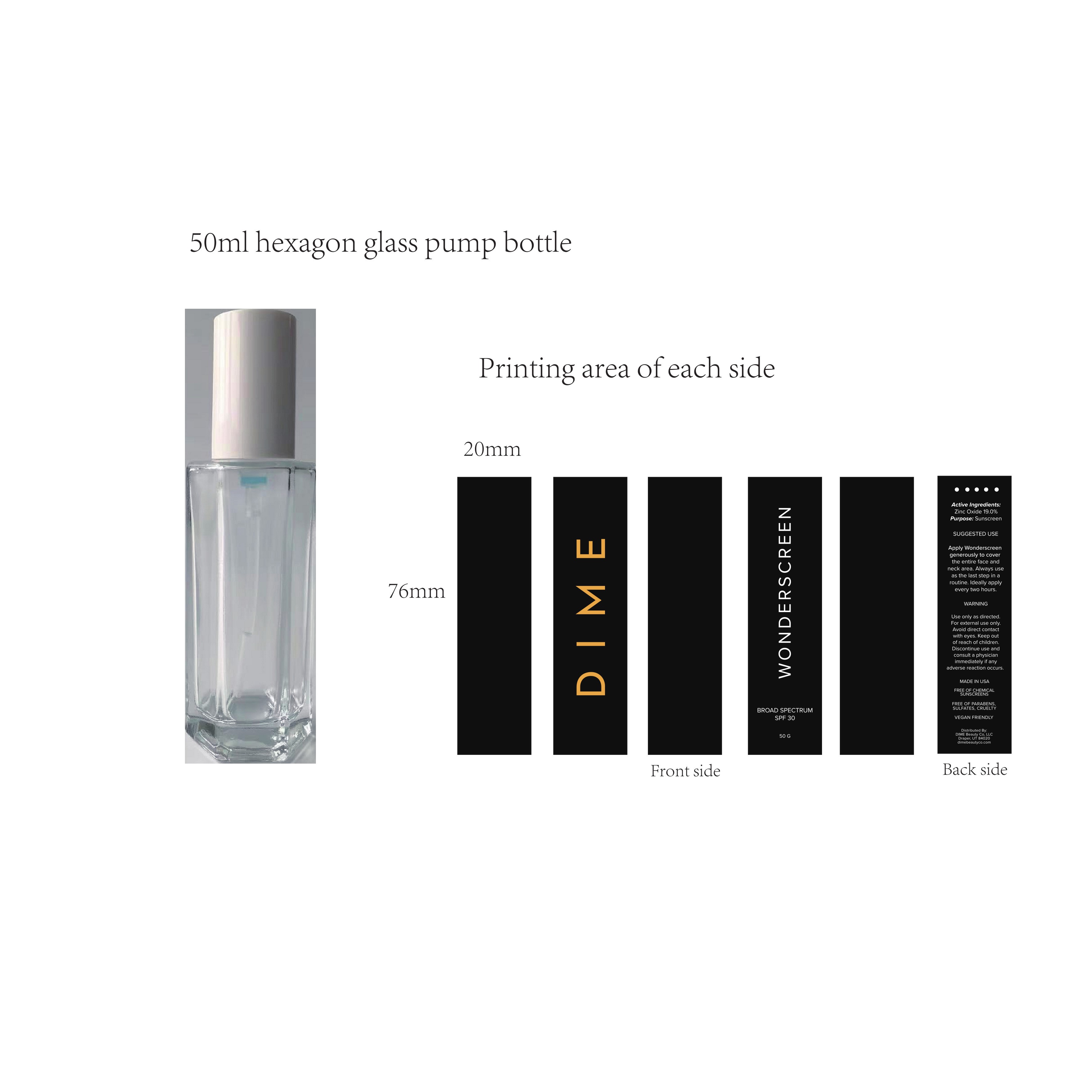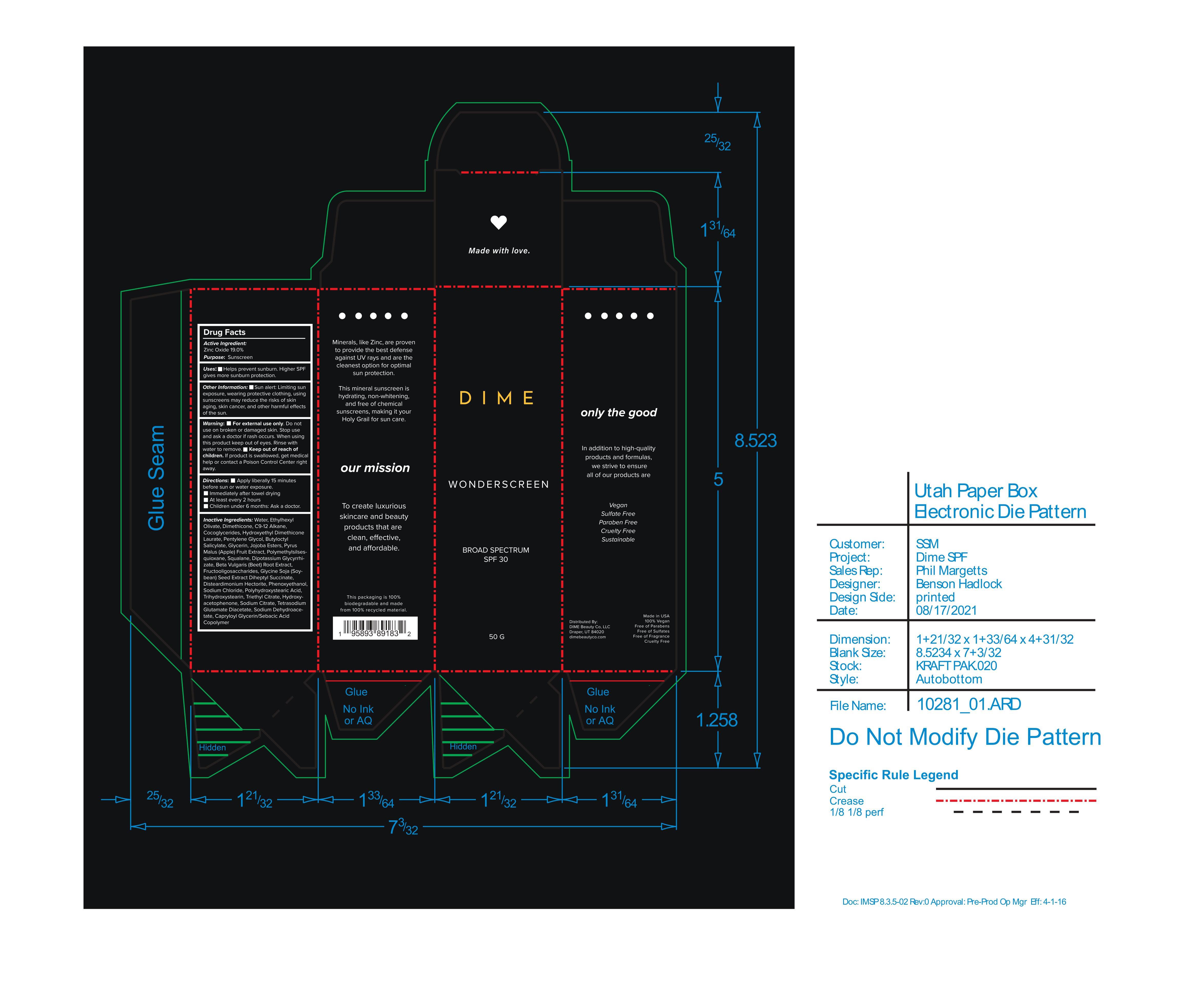 DRUG LABEL: Wonderscreen Broad Spectrum SPF 30
NDC: 44717-062 | Form: CREAM
Manufacturer: Wasatch Product Development, LLC.
Category: otc | Type: HUMAN OTC DRUG LABEL
Date: 20251010

ACTIVE INGREDIENTS: ZINC OXIDE 19 g/100 g
INACTIVE INGREDIENTS: TRIHYDROXYSTEARIN; PENTYLENE GLYCOL; DIMETHICONE 100; DISTEARDIMONIUM HECTORITE; SODIUM CITRATE; SODIUM CHLORIDE; HYDROXYACETOPHENONE; SQUALANE; GLYCYRRHIZINATE DIPOTASSIUM; BEET; WATER; BUTYLOCTYL SALICYLATE; GLYCERIN; APPLE; POLYMETHYLSILSESQUIOXANE (4.5 MICRONS); PHENOXYETHANOL; TETRASODIUM GLUTAMATE DIACETATE; TRIETHYL CITRATE; SODIUM DEHYDROACETATE; CAPRYLOYL GLYCERIN/SEBACIC ACID COPOLYMER (2000 MPA.S); POLYHYDROXYSTEARIC ACID (2300 MW); COCO-GLYCERIDES

Wonderscreen Broad Spectrum SPF 30

Active Ingredient: Zinc Oxide

Purpose: Sunscreen

PURPOSE

Uses: Helps prevent sunburn. Higher SPF gives more sunburn protection

Keep out of reach of children. If product is swallowed, get medical help or contact a Poison Control Center right away.

Stop use and ask a doctor if rash occurs.

Warning:

- For External use only. Do not use on broken or damaged skin

Directions:

- Apply liberally 15 minutes before sun or water exposure
- Immediately after towel drying
- At least every 2 hours
- Children under 6 months: ask a doctor

INACTIVE INGREDIENT

Inactive Ingredients: Water, Ethylhexyl Olivate, Dimethicone, C9-12 Alkane, Cocoglycerides, Hydroxyethyl Dimethicone Laurate, Pentylene Glycol, Butyloctyl Salicylate, Glycerin, Jojoba Esters, Pyrus Malus (Apple) Fruit Extract, Polymethylsilsesquioxane, Squalane, Dipotassium Glycyrrhizate, Beta Vulgaris (Beet) Root Extract, Fructooligosaccharides, Glycine Soja (Soybean) Seed Extract Diheptyl Succinate, Disteardimonium Hectorite, Phenoxyethanol, Sodium Chloride, Polyhydroxystearic Acid, Trihydroxystearin, Triethyl Citrate, Hydroxyacetophenone, Sodium Citrate, Tetrasodium Glutamate Diacetate, Sodium Dehydroacetate, Capryloyl Glycerin/Sebacic Acid Copolymer

PACKAGE LABEL

DIME

Wonderscreen

Broad Spectrum SPF 30

50 G